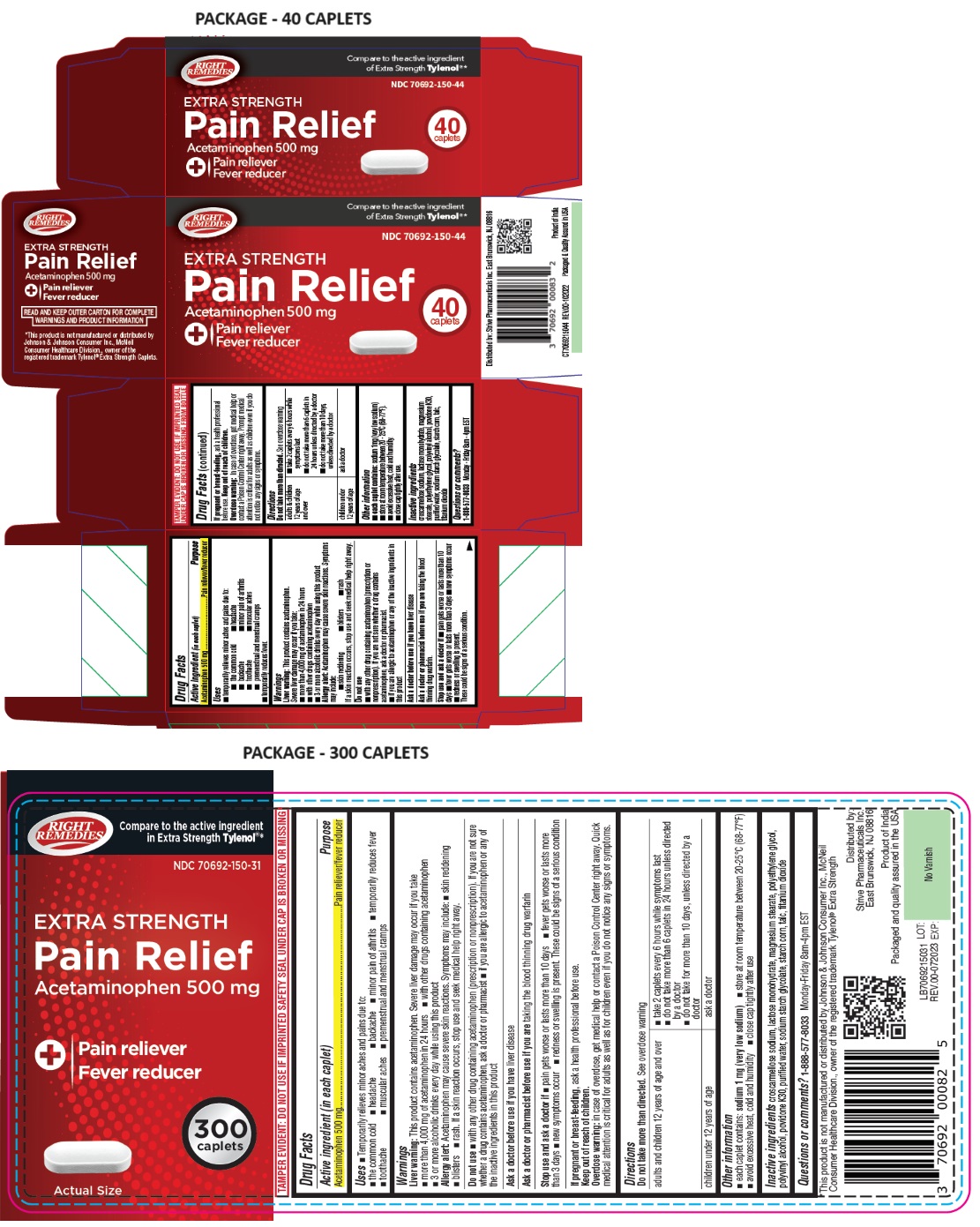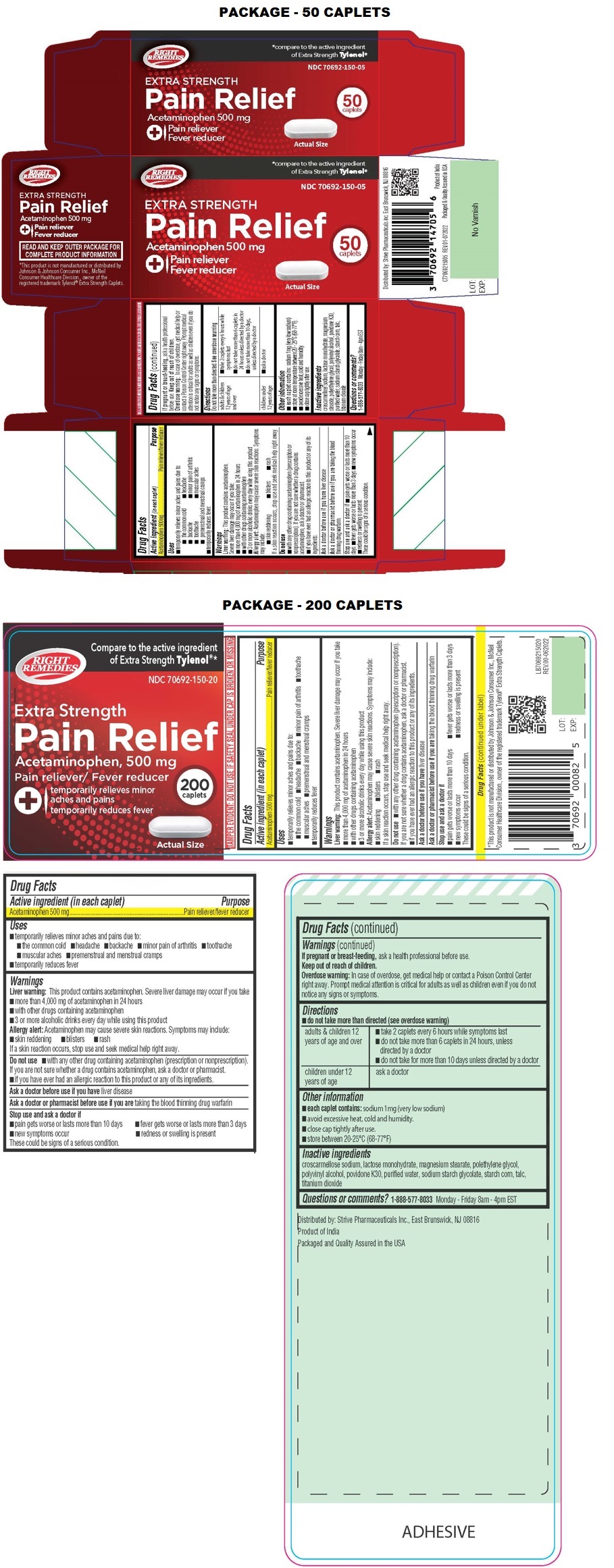 DRUG LABEL: RIGHT REMEDIES Pain Relief Extra Strength Caplet
NDC: 70692-150 | Form: TABLET, COATED
Manufacturer: Strive Pharmaceuticals Inc.
Category: otc | Type: HUMAN OTC DRUG LABEL
Date: 20231121

ACTIVE INGREDIENTS: ACETAMINOPHEN 500 mg/1 1
INACTIVE INGREDIENTS: CROSCARMELLOSE SODIUM; LACTOSE MONOHYDRATE; MAGNESIUM STEARATE; POLYETHYLENE GLYCOL, UNSPECIFIED; POLYVINYL ALCOHOL, UNSPECIFIED; POVIDONE K30; WATER; SODIUM STARCH GLYCOLATE TYPE A; STARCH, CORN; TALC; TITANIUM DIOXIDE

RIGHT REMEDIES Pain Relief EXTRA STRENGTH Caplet

Active Ingredient (in each caplet)

Acetaminophen 500mg

Purpose

Pain reliever/fever reducer

Uses

• temporarily relieves minor aches and pains due to:
• the common cold • headache
• backache • minor pain of arthritis
• toothache • muscular aches
• premenstrual and menstrual cramps
• temporarily reduces fever.

Warnings

Liver warning: This product contains acetaminophen.
Severe liver damage may occur if you take:
• more than 4,000 mg of acetaminophen in 24 hours
• with other drugs containing acetaminophen
• 3 or more alcoholic drinks every day while using this product

Allergy Alert: Acetaminophen may cause severe skin reactions. Symptoms may include:
• skin reddening • blisters • rash
If a skin reaction occurs, stop use and seek medical help right away.

Do not use
• with any other drug containing acetaminophen (prescription or nonprescription). If you are not sure whether a drug contains acetaminophen, ask a doctor or pharmacist.
• if you have ever had an allergic reaction to this product or any of its ingredients.

Ask a doctor before use if you have liver disease
Ask a doctor or pharmacist before use if you are taking the blood thinning drug warfarin.

Stop use and ask a doctor if • pain gets worse or lasts more than 10 days • fever gets worse or lasts more than 3 days • new symptoms occur • redness or swelling is present.
These could be signs of a serious condition.

If pregnant or breast-feeding, ask a health professional before use.

Keep out of reach of children.
Overdose warning: In case of overdose, get medical help or contact a Poison Control Center right away. Prompt medical attention is critical for adults as well as children even if you do not notice any signs or symptoms.

Directions

Do not take more than directed. See overdose warning

adult & children 12 years of age and over | • take 2 caplets every 6 hours while symptoms last; • do not take more than 6 caplets in 24 hours unless directed by a doctor; • do not take more than 10 days, unless directed by a doctor
children under; 12 years of age | • ask a doctor

Other information

• each caplet contains: sodium 1 mg (very low sodium)
• store at room temperature between 20 - 25ºC (68-77ºF).
• avoid excessive heat, cold and humidity.
• close cap tightly after use.

Inactive ingredients

croscarmellose sodium, lactose monohydrate, magnesium stearate, polyethylene glycol, polyvinyl alcohol, povidone k30, purified water, sodium starch glycolate, starch corn, talc, titanium dioxide

Questions or comments?

1-888-577-8033 Monday - Friday 8am - 4pm EST

*compare to the active ingredient of Extra Strength Tylenol®

TAMPER EVIDENT. DO NOT USE IF IMPRINTED SEAL UNDER CAP IS BROKEN OR MISSING FROM BOTTLE

Distributed by: Strive Pharmaceuticals inc. East Brunswick, NJ 08816

Product of India

Packaged & Quality Assured in USA

READ AND KEEP OUTER PACKAGE FOR COMPLETE PRODUCT INFORMATION

*This product is not manufactured or distributed by Johnson & Johnson Consumer Inc., McNeil Consumer Healthcare Division., owner of the registered trademark Tylenol® Extra Strength Caplets.

REV.00- 102022